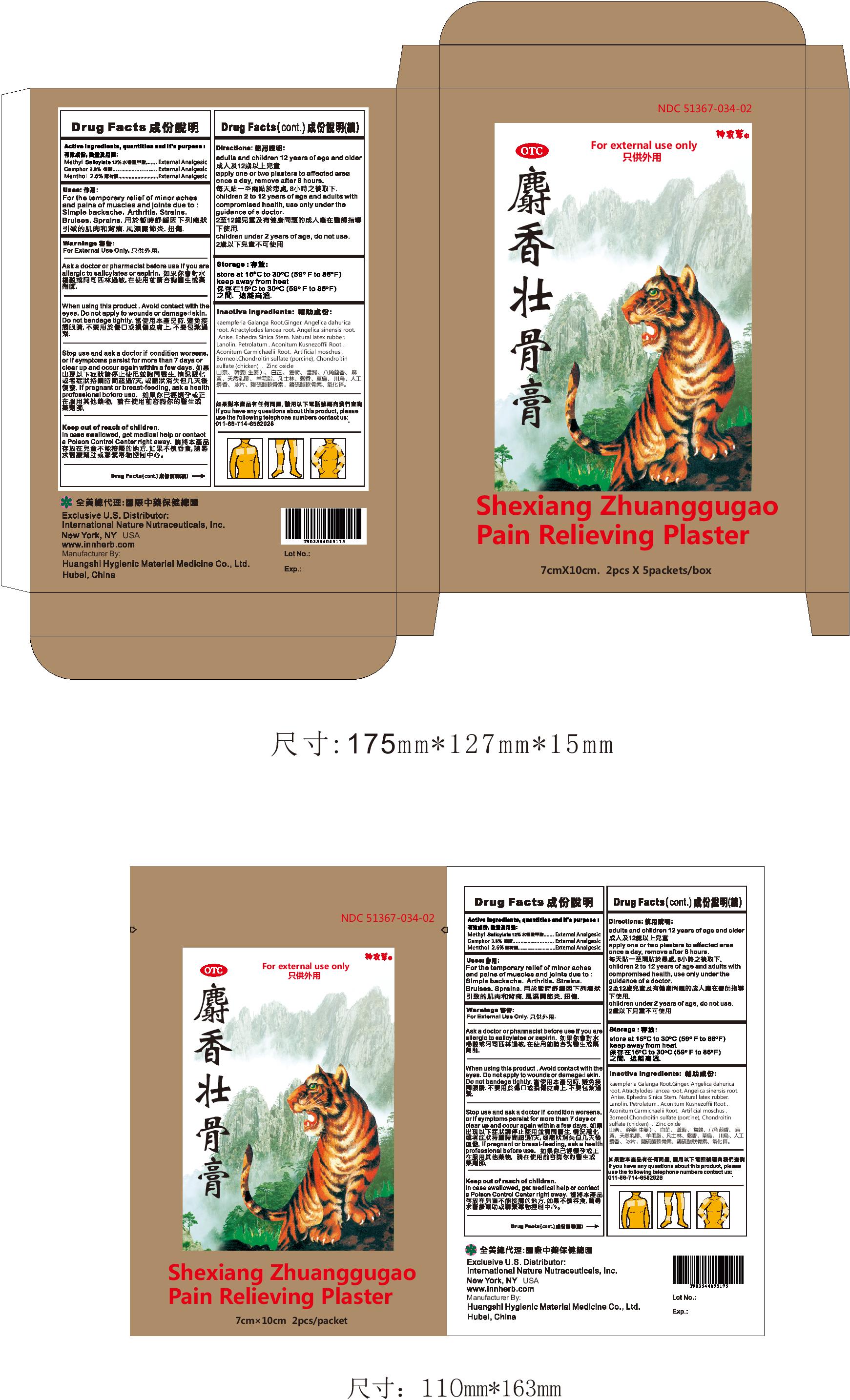 DRUG LABEL: Shexiang Zhuanggugao
NDC: 51367-034 | Form: PLASTER
Manufacturer: International Nature Nutraceuticals
Category: otc | Type: HUMAN OTC DRUG LABEL
Date: 20241219

ACTIVE INGREDIENTS: Camphor (Synthetic) 21.78 mg/1 1; METHYL SALICYLATE 29 mg/1 1; MENTHOL, UNSPECIFIED FORM 18.67 mg/1 1
INACTIVE INGREDIENTS: KAEMPFERIA GALANGA ROOT; GINGER; ANGELICA DAHURICA ROOT; ATRACTYLODES LANCEA ROOT; ANGELICA SINENSIS ROOT; ANISE; EPHEDRA SINICA STEM; NATURAL LATEX RUBBER; LANOLIN; PETROLATUM; ROSIN; ACONITUM KUSNEZOFFII ROOT; ACONITUM CARMICHAELII ROOT; MOSCHUS MOSCHIFERUS WHOLE; BORNEOL; CHONDROITIN SULFATE (PORCINE); CHONDROITIN SULFATE (CHICKEN); ZINC OXIDE

Shexiang Zhuanggugao
Pain Relieving Plaster

Drug Facts

Active Ingredients, quantities and it's purpose :

Methyl Salicylate
Camphor
Methnol

Uses:

For the temporary relief of minor aches

and pains of muscles and joints due to :

Simple backache. Arthritis. Strains.

Bruises. Sprains.

Warnings:

When using this product. Avoid contact with the

eyes. Do not apply to wounds or damges skin.

Do not bandage tightly.

Warnings:

Ask a doctor or pharmacist before use if you are

allergic to salicylates or aspirin.

Warnings:

Stop use and ask a doctor if condition worsens,

or if symptoms persist for more than 7 days or

clear up and occur again within a few days.

If pregnant or breast-feeding, ask a health

professional before use.

Inactive Ingredients:

If you have any questions about this product, please

use the following telephone numbers to contact us:

011-86-714-6582928

Keep out of reach of children

In case swallowed, get medical help or contact

a Poison Control Center right away.

Warnings:

For External Use Only.

Directions:

adults and children 12 years of age and older

apply one or two plasters to affected area

once a day, remove after 8 hours.

children 2 to 12 years of age and adults with

compromised health, use only under the

guidance of a doctor.

children under 2 years of age, do not use.

Uses:

For the temporary relief of minor aches

and pains of muscles and joints due to :

Simple backache. Arthritis. Strains.

Bruises. Sprains.

Inactive Ingredients:

kaempferia Galanga Root.Ginger. Angelica dahurica
root. Atractylodes lancea root. Angelica sinensis root.
Anise. Ephedra Sinica Stem. Natural latex rubber.
Lanolin. Petrolatum . Aconitum Kusnezoffii Root .
Aconitum Carmichaelii Root. Artificial moschus .
Borneol.Chondroitin sulfate (porcine), Chondroitin
sulfate (chicken) . Zinc oxide

Storage:

store at 15 C to 30 C (59 F to 86 F)

keep away from heat